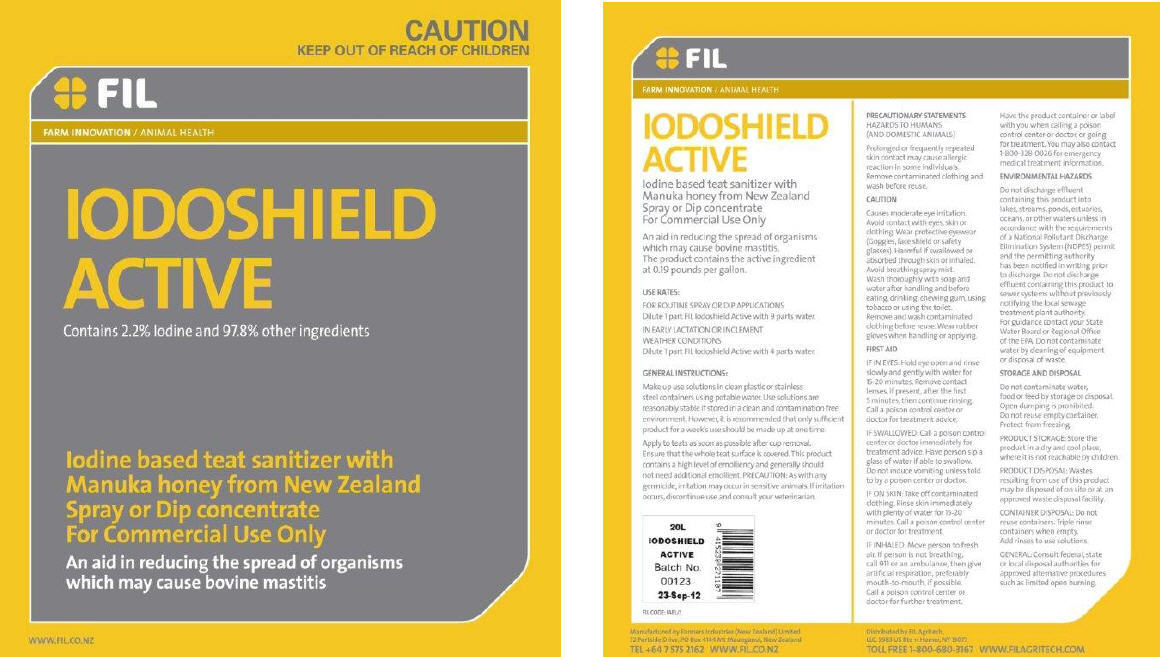 DRUG LABEL: Iodoshield Active
NDC: 51546-001 | Form: CONCENTRATE
Manufacturer: Farmers Industries (New Zealand) Limited
Category: animal | Type: OTC ANIMAL DRUG LABEL
Date: 20100818

ACTIVE INGREDIENTS: iodine 86.2 g/4.55 L
INACTIVE INGREDIENTS: sorbitol; honey; water; lanolin; alcohol

IODOSHIELD
ACTIVE

Iodine based teat sanitizer with Manuka honey from New Zealand
Spray or Dip concentrate
For Commercial Use Only

An aid in reducing the spread of organisms which may cause bovine mastitis.
The product contains the active ingredient at 0.19 pounds per gallon.

USE RATES

FOR ROUTINE SPRAY OR DIP APPLICATIONS
Dilute 1 part FIL Iodoshield Active with 9 parts water.

IN EARLY LACTATION OR INCLEMENT WEATHER CONDITIONS
Dilute 1 part FIL Iodoshield Active with 4 parts water.

GENERAL INSTRUCTIONS

Make up use solutions in clean plastic or stainless steel containers using potable water. Use solutions are reasonably stable if stored in a clean and contamination free environment. However, it is recommended that only sufficient product for a week's use should be made up at one time.

Apply to teats as soon as possible after cup removal. Ensure that the whole teat surface is covered. This product contains a high level of emolliency and generally should not need additional emollient. PRECAUTION: As with any germicide, irritation may occur in sensitive animals. If irritation occurs, discontinue use and consult your veterinarian.

PRECAUTIONARY STATEMENTS

HAZARDS TO HUMANS (AND DOMESTIC ANIMALS)

Prolonged or frequently repeated skin contact may cause allergic reaction in some individuals. Remove contaminated clothing and wash before reuse.

CAUTION

Causes moderate eye irritation. Avoid contact with eyes, skin or clothing. Wear protective eyewear (Goggles, face shield or safety glasses). Harmful if swallowed or absorbed through skin or inhaled. Avoid breathing spray mist. Wash thoroughly with soap and water after handling and before eating, drinking, chewing gum, using tobacco or using the toilet. Remove and wash contaminated clothing before reuse. Wear rubber gloves when handling or applying.

FIRST AID

IF IN EYES: Hold eye open and rinse slowly and gently with water for 15-20 minutes. Remove contact lenses, if present, after the first 5 minutes, then continue rinsing. Call a poison control center or doctor for treatment advice.

IF SWALLOWED: Call a poison control center or doctor immediately for treatment advice. Have person sip a glass of water if able to swallow. Do not induce vomiting unless told to by a poison center or doctor.

IF ON SKIN: Take off contaminated clothing. Rinse skin immediately with plenty of water for 15-20 minutes. Call a poison control center or doctor for treatment.

IF INHALED: Move person to fresh air. If person is not breathing, call 911 or an ambulance, then give artificial respiration, preferably mouth-to-mouth, if possible. Call a poison control center or doctor for further treatment.

Have the product container or label with you when calling a poison control center or doctor, or going for treatment. You may also contact 1-800-328-0026 for emergency medical treatment information.

ENVIRONMENTAL HAZARDS

Do not discharge effluent containing this product into lakes, streams, ponds, estuaries, oceans, or other waters unless in accordance with the requirements of a National Pollutant Discharge Elimination System (NDPES) permit and the permitting authority has been notified in writing prior to discharge. Do not discharge effluent containing this product to sewer systems without previously notifying the local sewage treatment plant authority.

For guidance contact your State Water Board or Regional Office of the EPA. Do not contaminate water by cleaning of equipment or disposal of waste.

STORAGE AND DISPOSAL

Do not contaminate water, food or feed by storage or disposal. Open dumping is prohibited. Do not reuse empty container. Protect from freezing.

PRODUCT STORAGE: Store the product in a dry and cool place, where it is not reachable by children.

PRODUCT DISPOSAL: Wastes resulting from use of this product may be disposed of on site or at an approved waste disposal facility.

CONTAINER DISPOSAL: Do not reuse containers. Triple rinse containers when empty. Add rinses to use solutions.

GENERAL: Consult federal, state, or local disposal authorities for approved alternative procedures such as limited open burning.

Manufactured by: Farmers Industries (New Zealand) Limited, 72 Portside Drive, PO Box 4144 Mt Maunganui, New Zealand.

TEL +64 7 575 2162 WWW.FIL.CO.NZ

Distributed by FIL Agritech, LLC 5983 US Rte 11 Homer, NY 13077

TOLL FREE 1-800-680-3167 WWW.FILAGRITECH.COM

PRINCIPAL DISPLAY PANEL - 20 L Bottle Label

CAUTION
KEEP OUT OF REACH OF CHILDREN

FIL

FARM INNOVATION / ANIMAL HEALTH

IODOSHIELD
ACTIVE

Contains 2.2% Iodine and 97.8% other ingredients

Iodine based teat sanitizer with
Manuka honey from New Zealand
Spray or Dip concentrate
For Commercial Use Only

An aid in reducing the spread of organisms
which may cause bovine mastitis

WWW.FIL.CO.NZ